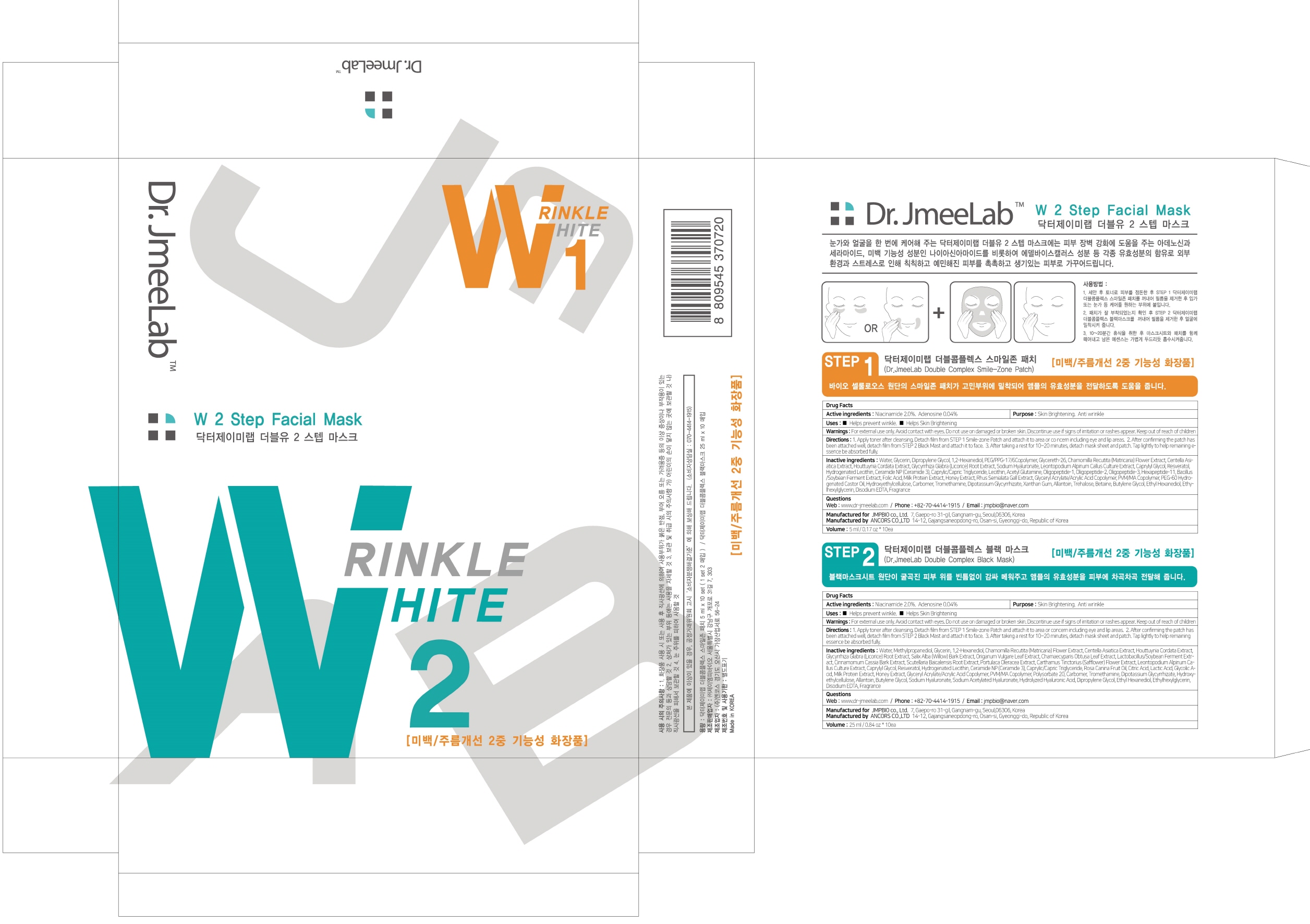 DRUG LABEL: Dr JmeeLab Double Complex Black Mask
NDC: 72144-020 | Form: PATCH
Manufacturer: JMPBIO co., Ltd.
Category: otc | Type: HUMAN OTC DRUG LABEL
Date: 20181229

ACTIVE INGREDIENTS: Niacinamide 0.50 g/25 mL; Adenosine 0.01 g/25 mL
INACTIVE INGREDIENTS: Water; Methylpropanediol

ACTIVE INGREDIENT

Active ingredients: Niacinamide 2.0%, Adenosine 0.04%

INACTIVE INGREDIENT

Inactive ingredients:

Water, Methylpropanediol, Glycerin, 1,2-Hexanediol, Chamomilla Recutita (Matricaria) Flower Extract, Centella Asiatica Extract, Houttuynia Cordata Extract, Glycyrrhiza Glabra (Licorice) Root Extract, Salix Alba (Willow) Bark Extract, Origanum Vulgare Leaf Extract, Chamaecyparis Obtusa Leaf Extract, Lactobacillus/Soybean Ferment Extract, Cinnamomum Cassia Bark Extract, Scutellaria Baicalensis Root Extract, Portulaca Oleracea Extract, Carthamus Tinctorius (Safflower) Flower Extract, Leontopodium Alpinum Callus Culture Extract, Caprylyl Glycol, Resveratol, Hydrogenated Lecithin, Ceramide NP (Ceramide 3), Caprylic/Capric Triglyceride, Rosa Canina Fruit Oil, Citric Acid, Lactic Acid, Glycolic Acid, Milk Protein Extract, Honey Extract, Glyceryl Acrylate/Acrylic Acid Copolymer, PVM/MA Copolymer, Polysorbate 20, Carbomer, Tromethamine, Dipotassium Glycyrrhizate, Hydroxyethylcellulose, Allantoin, Butylene Glycol, Sodium Hyaluronate, Sodium Acetylated Hyaluronate, Hydrolyzed Hyaluronic Acid, Dipropylene Glycol, Ethyl Hexanediol, Ethylhexylglycerin, Disodium EDTA, Fragrance

PURPOSE

Purpose: Skin Brightening, Anti wrinkle

WARNINGS

For external use only Avoid contact with eyes. Do not use on damaged or broken skin. Discontinue use if signs of irritation or rashes appear. Keep out of reach of children

KEEP OUT OF REACH OF CHILDREN

Uses

- Helps prevent winkle

- Helps Skin Brightening

Directions

1. Apply toner after cleansing. Detach film from STEP 1 Smile-zone Patch and attach it to area or concern including eye and lip areas.

2. After confirming the patch has been attached well, detach film from STEP 2 Black Mast and attach it to face.

3. After taking a rest for 10~20 minutes, detach mask sheet and patch. Tap lightly to help remaining essence be absorbed fully.